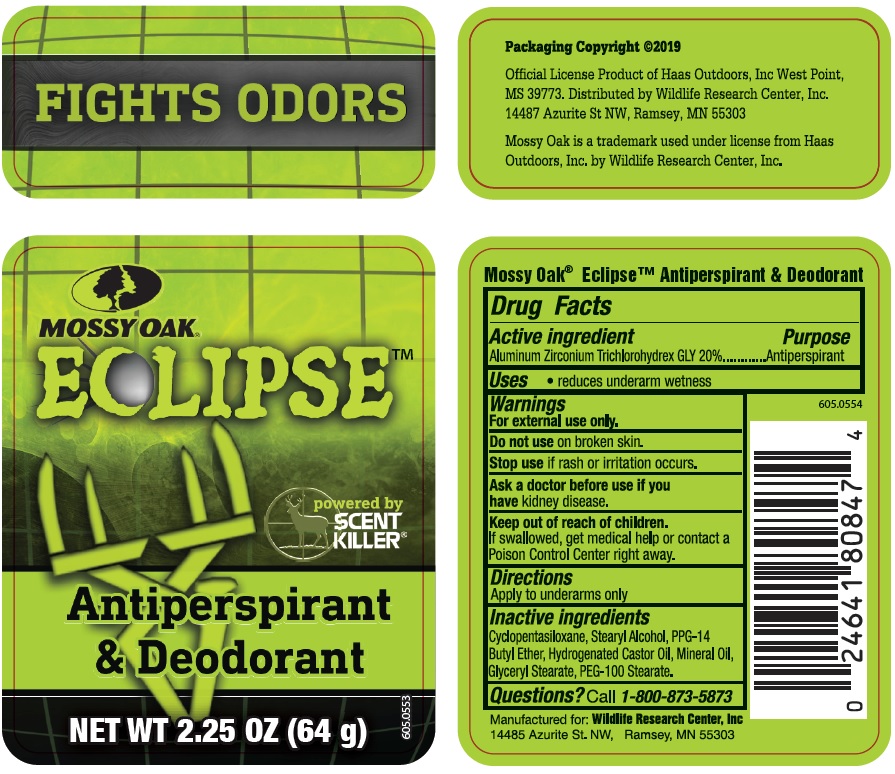 DRUG LABEL: Mossy Oak Eclipse
NDC: 10889-427 | Form: STICK
Manufacturer: VVF Kansas Services LLC
Category: otc | Type: HUMAN OTC DRUG LABEL
Date: 20191113

ACTIVE INGREDIENTS: ALUMINUM ZIRCONIUM TRICHLOROHYDREX GLY 12.8 g/64 g
INACTIVE INGREDIENTS: PPG-14 BUTYL ETHER; GLYCERYL STEARATE SE; CYCLOMETHICONE 5; STEARYL ALCOHOL; HYDROGENATED CASTOR OIL; MINERAL OIL; PEG-100 STEARATE

Mossy Oak Eclipse
Antiperspirant & Deodorant

Active Ingredient

Aluminum Zirconium Trichlorohydrex GLY 20%

Purpose

Antiperspirant

Use

- reduces underarm wetness

Warnings

For external use only.

Do not use on broken skin.

Stop use if rash or irritation occurs.

Ask a doctor before use if you have kidney disease.

Keep out of reach of children.

If swallowed, get medical help or contact a Poison Control Center right away.

Directions

Apply to underarms only

Inactive Ingredients

Cyclopentasiloxane, Stearyl Alcohol, PPG-14

Butyl Ether, Hydrogenated Castor Oil, Mineral Oil,

Glyceryl Stearate, PEG-100 Stearate.

Questions?

Call 1-800-873-5873

Mossy Oak Eclipse™ Antiperspirant & Deodorant

Manufactured for: Wildlife Research Center, Inc

14485 Azurite St. NW, Ramsey, MN 55303

UPC: 0-24641-80847-4

Packaging Copyright ©2019

Official License Product of Haas Outdoors, Inc. West Point,

MS 39773. Distributed by Wildlife Research Center, Inc.

14487 Azurite St NW, Ramsey, MN 55303

Mossy Oak is a trademark used under license from Haas

Outdoors, Inc. by Wildlife Research Center, Inc.

Mossy Oak Eclipse™

Antiperspirant & Deodorant

Powered by Scent Killer

NET WT 2.25 OZ (64 g)

Fights Odors